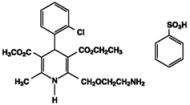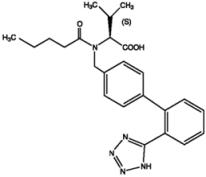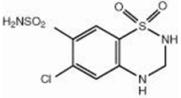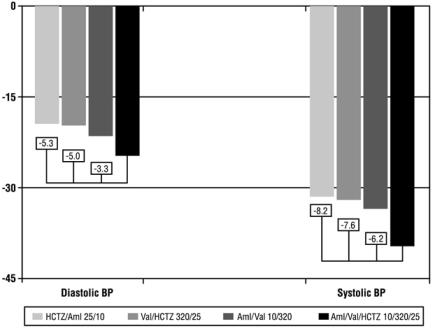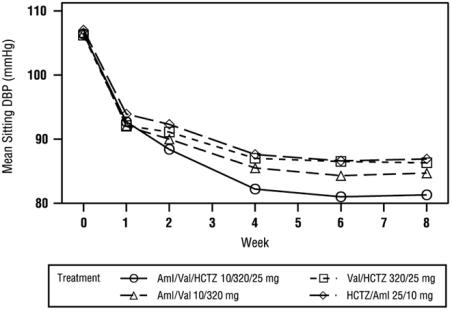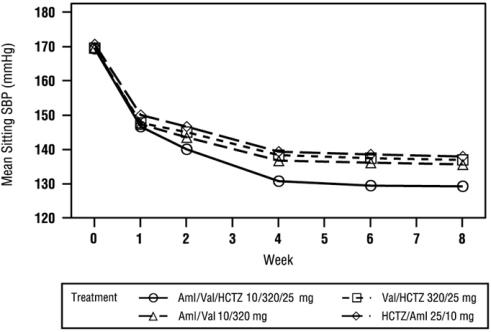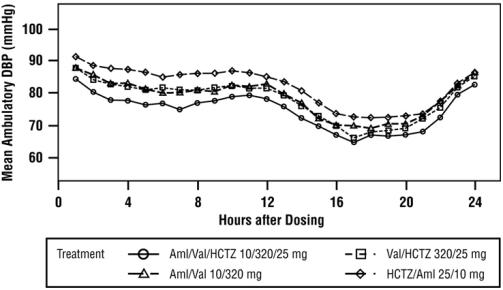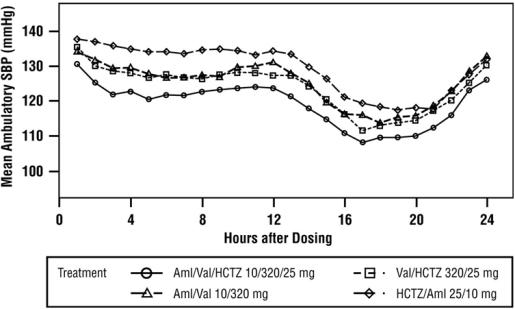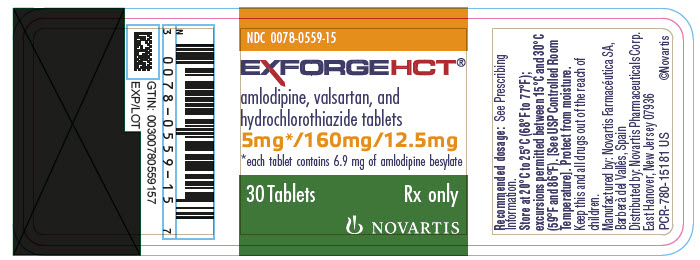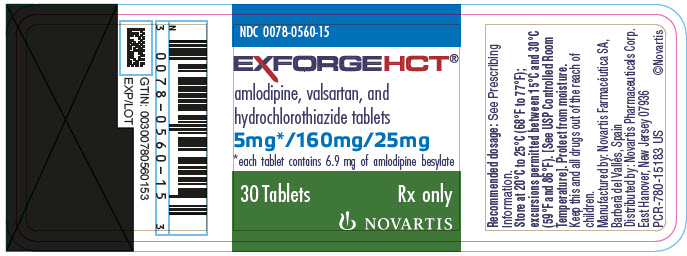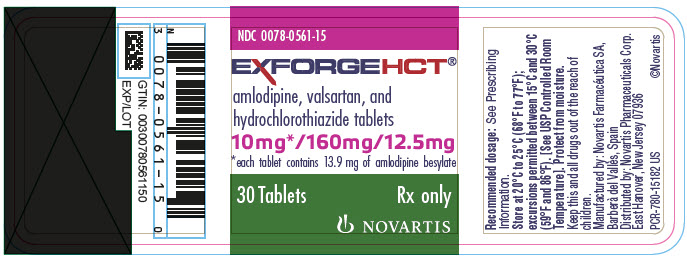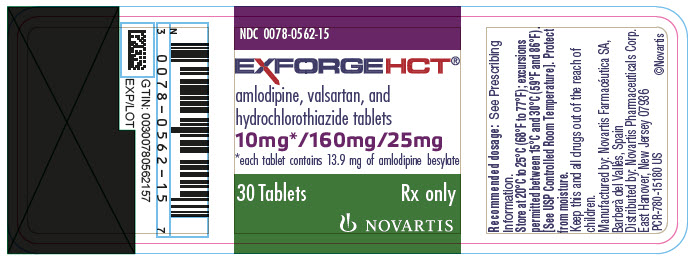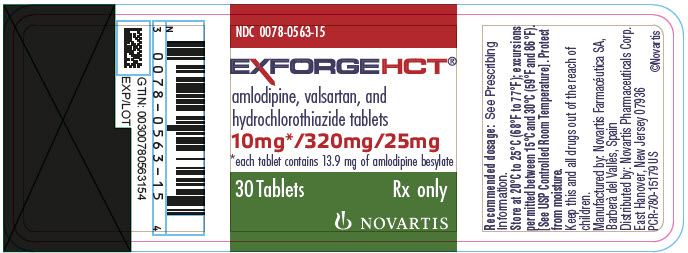 DRUG LABEL: Exforge HCT
NDC: 0078-0559 | Form: TABLET, FILM COATED
Manufacturer: Novartis Pharmaceuticals Corporation
Category: prescription | Type: HUMAN PRESCRIPTION DRUG LABEL
Date: 20251212

ACTIVE INGREDIENTS: AMLODIPINE BESYLATE 5 mg/1 1; VALSARTAN 160 mg/1 1; HYDROCHLOROTHIAZIDE 12.5 mg/1 1
INACTIVE INGREDIENTS: SILICON DIOXIDE; CROSPOVIDONE; HYPROMELLOSES; MAGNESIUM STEARATE; CELLULOSE, MICROCRYSTALLINE; TALC; TITANIUM DIOXIDE

HIGHLIGHTS OF PRESCRIBING INFORMATION

These highlights do not include all the information needed to use EXFORGE HCT safely and effectively. See full prescribing information for EXFORGE HCT.
EXFORGE HCT® (amlodipine, valsartan, and hydrochlorothiazide) tablets, for oral use
Initial U.S. Approval: 2009

WARNING: FETAL TOXICITY

See full prescribing information for complete boxed warning.

- When pregnancy is detected, discontinue Exforge HCT as soon as possible. (5.1)
- Drugs that act directly on the renin-angiotensin system can cause injury and death to the developing fetus. (5.1)

1 INDICATIONS AND USAGE

Exforge HCT is a combination tablet of amlodipine, a dihydropyridine calcium channel blocker (DHP CCB), valsartan, an angiotensin II receptor blocker (ARB), and hydrochlorothiazide, a thiazide diuretic. Exforge HCT is indicated for the treatment of hypertension to lower blood pressure. Lowering blood pressure reduces the risk of fatal and nonfatal cardiovascular events, primarily strokes, and myocardial infarctions. (1)

Limitations of Use

Exforge HCT is not indicated for initial treatment of hypertension. (1)

2 DOSAGE AND ADMINISTRATION

- Dose once-daily. Titrate up to a maximum dose of 10/320/25 mg. (2.1)
- Exforge HCT may be used as add-on/switch therapy for patients not adequately controlled on any two of the following antihypertensive classes: calcium channel blockers, angiotensin receptor blockers, and diuretics. (2.2)
- Exforge HCT may be substituted for its individually titrated components. (2.3)

3 DOSAGE FORMS AND STRENGTHS

Tablets: (amlodipine/valsartan/hydrochlorothiazide mg) 5/160/12.5, 10/160/12.5, 5/160/25, 10/160/25, 10/320/25 (3)

4 CONTRAINDICATIONS

- Anuria (4)
- Hypersensitivity to sulfonamide-derived drugs (4)
- Known hypersensitivity to any component (4)
- Do not coadminister aliskiren with Exforge HCT in patients with diabetes (4)

5 WARNINGS AND PRECAUTIONS

- Hypotension: Correct volume depletion prior to initiation (5.2)
- Increased angina and/or myocardial infarction (5.3)
- Monitor renal function and potassium in susceptible patients (5.4, 5.5)
- Exacerbation or activation of systemic lupus erythematosus (5.7)
- Observe for signs of fluid or electrolyte imbalance (5.9)
- Acute angle-closure glaucoma (5.10)

6 ADVERSE REACTIONS

Most common adverse events (≥ 2% incidence) are dizziness, peripheral edema, headache, dyspepsia, fatigue, muscle spasms, back pain, nausea, and nasopharyngitis. (6.1)

To report SUSPECTED ADVERSE REACTIONS, contact Novartis Pharmaceuticals Corporation at 1-888-669-6682 or FDA at 1-800-FDA-1088 or www.fda.gov/medwatch.

7 DRUG INTERACTIONS

- If simvastatin is coadministered with amlodipine, do not exceed doses greater than 20 mg daily of simvastatin. (7)
- Antidiabetic drugs: Dosage adjustment of antidiabetic may be required. (7)
- Cholestyramine and Colestipol: Reduced absorption of thiazides. (12.3)
- Lithium: Increased risk of lithium toxicity. Monitor serum lithium concentrations during concurrent use. (7)
- Non-Steroidal Anti-Inflammatory Drug (NSAID) use may lead to increased risk of renal impairment and loss of anti-hypertensive effect. (7)
- Dual inhibition of the renin-angiotensin system: Increased risk of renal impairment, hypotension, and hyperkalemia. (7)

8 USE IN SPECIFIC POPULATIONS

Lactation: Breastfeeding is not recommended (8.2)

Geriatric Patients: Not recommended for initial therapy (8.5)

Hepatic Impairment: Not recommended for initial therapy (8.7)

FULL PRESCRIBING INFORMATION

WARNING: FETAL TOXICITY

- When pregnancy is detected, discontinue Exforge HCT as soon as possible. (5.1)
- Drugs that act directly on the renin-angiotensin system can cause injury and death to the developing fetus. (5.1)

1 INDICATIONS AND USAGE

Exforge HCT (amlodipine, valsartan, and hydrochlorothiazide) is indicated for the treatment of hypertension, to lower blood pressure. Lowering blood pressure reduces the risk of fatal and nonfatal cardiovascular events, primarily strokes and myocardial infarctions. These benefits have been seen in controlled trials of antihypertensive drugs from a wide variety of pharmacologic classes, including amlodipine, hydrochlorothiazide, and the angiotensin II receptor blocker (ARB) class to which valsartan principally belongs. There are no controlled trials demonstrating risk reduction with Exforge HCT.

Control of high blood pressure should be part of comprehensive cardiovascular risk management, including, as appropriate, lipid control, diabetes management, antithrombotic therapy, smoking cessation, exercise, and limited sodium intake. Many patients will require more than 1 drug to achieve blood pressure goals. For specific advice on goals and management, see published guidelines, such as those of the National High Blood Pressure Education Program’s Joint National Committee on Prevention, Detection, Evaluation, and Treatment of High Blood Pressure (JNC).

Numerous antihypertensive drugs, from a variety of pharmacologic classes and with different mechanisms of action, have been shown in randomized controlled trials to reduce cardiovascular morbidity and mortality, and it can be concluded that it is blood pressure reduction, and not some other pharmacologic property of the drugs, that is largely responsible for those benefits. The largest and most consistent cardiovascular outcome benefit has been a reduction in the risk of stroke, but reductions in myocardial infarction and cardiovascular mortality also have been seen regularly.

Elevated systolic or diastolic pressure causes increased cardiovascular risk, and the absolute risk increase per mmHg is greater at higher blood pressures, so that even modest reductions of severe hypertension can provide substantial benefit. Relative risk reduction from blood pressure reduction is similar across populations with varying absolute risk, so the absolute benefit is greater in patients who are at higher risk independent of their hypertension (e.g., patients with diabetes or hyperlipidemia), and such patients would be expected to benefit from more aggressive treatment to a lower blood pressure goal.

Some antihypertensive drugs have smaller blood pressure effects (as monotherapy) in black patients, and many antihypertensive drugs have additional approved indications and effects (e.g., on angina, heart failure, or diabetic kidney disease). These considerations may guide selection of therapy.

Limitations of Use

Exforge HCT is not indicated for the initial therapy of hypertension [see Dosage and Administration (2)].

2 DOSAGE AND ADMINISTRATION

2.1 General Considerations

Dose once-daily. The dosage may be increased after 2 weeks of therapy. The full blood pressure lowering effect was achieved 2 weeks after being on the maximal dose of Exforge HCT. The maximum recommended dose of Exforge HCT is 10/320/25 mg.

2.2 Add-on/Switch Therapy

Exforge HCT may be used for patients not adequately controlled on any 2 of the following antihypertensive classes: calcium channel blockers, angiotensin receptor blockers, and diuretics.

A patient who experiences dose-limiting adverse reactions to an individual component while on any dual combination of the components of Exforge HCT may be switched to Exforge HCT containing a lower dose of that component to achieve similar blood pressure reductions.

2.3 Replacement Therapy

Exforge HCT may be substituted for the individually titrated components.

2.4 Use With Other Antihypertensive Drugs

Exforge HCT may be administered with other antihypertensive agents.

3 DOSAGE FORMS AND STRENGTHS

Exforge HCT tablets are available as follows:

- 5 mg amlodipine/160 mg valsartan/12.5 mg hydrochlorothiazide tablets – White, non-scored, film-coated tablet, ovaloid, biconvex with beveled edge with debossing “NVR” on one side and “VCL” on the other side.
- 10 mg amlodipine/160 mg valsartan/12.5 mg hydrochlorothiazide tablets – Pale yellow, non-scored, film-coated tablet, ovaloid, biconvex with beveled edge with debossing “NVR” on one side and “VDL” on the other side.
- 5 mg amlodipine/160 mg valsartan/25 mg hydrochlorothiazide tablets – Yellow, non-scored, film-coated tablet, ovaloid, biconvex with beveled edge with debossing “NVR” on one side and “VEL” on the other side.
- 10 mg amlodipine/160 mg valsartan/25 mg hydrochlorothiazide tablets – Brown-yellow, non-scored, film-coated tablet, ovaloid, biconvex with beveled edge with debossing “NVR” on one side and “VHL” on the other side.
- 10 mg amlodipine/320 mg valsartan/25 mg hydrochlorothiazide tablets – Brown-yellow, non-scored, film-coated tablet, ovaloid, biconvex with beveled edge with debossing “NVR” on one side and “VFL” on the other side.

4 CONTRAINDICATIONS

Do not use in patients with anuria, hypersensitivity to other sulfonamide-derived drugs, or hypersensitivity to any component of this product.

Do not coadminister aliskiren with Exforge HCT in patients with diabetes [see Drug Interactions (7)].

5 WARNINGS AND PRECAUTIONS

5.1 Fetal Toxicity

Valsartan

Exforge HCT can cause fetal harm when administered to a pregnant woman. Use of drugs that act on the renin-angiotensin system during the second and third trimesters of pregnancy reduces fetal renal function and increases fetal and neonatal morbidity and death. Resulting oligohydramnios can be associated with fetal lung hypoplasia and skeletal deformations. Potential neonatal adverse effects include skull hypoplasia, anuria, hypotension, renal failure, and death. When pregnancy is detected, discontinue Exforge HCT as soon as possible [see Use in Specific Populations (8.1)].

Hydrochlorothiazide

Thiazides cross the placenta, and use of thiazides during pregnancy is associated with fetal or neonatal jaundice, thrombocytopenia, and possibly other adverse reactions that have occurred in adults.

5.2 Hypotension in Volume- or Salt-Depleted Patients

Excessive hypotension, including orthostatic hypotension, was seen in 1.7% of patients treated with the maximum dose of Exforge HCT (10/320/25 mg) compared to 1.8% of valsartan/HCTZ (320/25 mg) patients, 0.4% of amlodipine/valsartan (10/320 mg) patients, and 0.2% of HCTZ/amlodipine (25/10 mg) patients in a controlled trial in patients with moderate to severe uncomplicated hypertension. In patients with an activated renin-angiotensin system, such as volume- or salt-depleted patients receiving high doses of diuretics, symptomatic hypotension may occur in patients receiving angiotensin receptor blockers. Correct this condition prior to administration of Exforge HCT.

Exforge HCT has not been studied in patients with heart failure, recent myocardial infarction, or in patients undergoing surgery or dialysis. Patients with heart failure or post-myocardial infarction who were given valsartan commonly have some reduction in blood pressure, but discontinuation of therapy because of continuing symptomatic hypotension usually is not necessary when dosing instructions are followed. In controlled trials in heart failure patients, the incidence of hypotension in valsartan-treated patients was 5.5% compared to 1.8% in placebo-treated patients. In the Valsartan in Acute Myocardial Infarction Trial (VALIANT), hypotension in post-myocardial infarction patients led to permanent discontinuation of therapy in 1.4% of valsartan-treated patients and 0.8% of captopril-treated patients.

Since the vasodilation induced by amlodipine is gradual in onset, acute hypotension has rarely been reported after oral administration. Do not initiate treatment with Exforge HCT in patients with aortic or mitral stenosis or obstructive hypertrophic cardiomyopathy.

If excessive hypotension occurs with Exforge HCT, place the patient in a supine position and, if necessary, give intravenous normal saline. A transient hypotensive response is not a contraindication to further treatment, which usually can be continued without difficulty once the blood pressure has stabilized.

5.3 Increased Angina and/or Myocardial Infarction

Worsening angina and acute myocardial infarction can develop after starting or increasing the dose of amlodipine, particularly in patients with severe obstructive coronary artery disease.

5.4 Impaired Renal Function

Changes in renal function, including acute renal failure can be caused by drugs that inhibit the renin-angiotensin system and by diuretics. Patients whose renal function may depend in part on the activity of the renin-angiotensin system (e.g., patients with renal artery stenosis, chronic kidney disease, severe congestive heart failure, or volume depletion) may be at particular risk of developing acute renal failure on Exforge HCT. Monitor renal function periodically in these patients. Consider withholding or discontinuing therapy in patients who develop a clinically significant decrease in renal function on Exforge HCT [see Drug Interactions (7)].

5.5 Potassium Abnormalities

In the controlled trial of Exforge HCT in moderate to severe hypertensive patients, the incidence of hypokalemia (serum potassium < 3.5 mEq/L) at any time post-baseline with the maximum dose of Exforge HCT (10/320/25 mg) was 10% compared to 25% with HCTZ/amlodipine (25/10 mg), 7% with valsartan/HCTZ (320/25 mg), and 3% with amlodipine/valsartan (10/320 mg). One patient (0.2%) discontinued therapy due to an adverse event of hypokalemia in each of the Exforge HCT and HCTZ/amlodipine groups. The incidence of hyperkalemia (serum potassium > 5.7 mEq/L) was 0.4% with Exforge HCT compared to 0.2% to 0.7% with the dual therapies.

Some patients with heart failure have developed increases in potassium on valsartan. These effects are usually minor and transient, and they are more likely to occur in patients with pre-existing renal impairment. Dosage reduction and/or discontinuation of the diuretic and/or valsartan may be required.

Hydrochlorothiazide can cause hypokalemia and hyponatremia. Hypomagnesemia can result in hypokalemia which appears difficult to treat despite potassium repletion. Drugs that inhibit the renin-angiotensin system can cause hyperkalemia. Monitor serum electrolytes periodically.

If hypokalemia is accompanied by clinical signs (e.g., muscular weakness, paresis, or ECG alterations), Exforge HCT should be discontinued. Correction of hypokalemia and any coexisting hypomagnesemia is recommended prior to the initiation of thiazides.

5.6 Hypersensitivity Reaction

Hypersensitivity reactions to hydrochlorothiazide may occur in patients with or without a history of allergy or bronchial asthma, but are more likely in patients with such a history.

5.7 Systemic Lupus Erythematosus

Thiazide diuretics have been reported to cause exacerbation or activation of systemic lupus erythematosus.

5.8 Lithium Interaction

Increases in serum lithium concentrations and lithium toxicity have been reported with concomitant use of valsartan or thiazide diuretics. Monitor lithium levels in patients receiving Exforge HCT and lithium [see Drug Interactions (7)].

5.9 Metabolic Imbalances

Hydrochlorothiazide may alter glucose tolerance and raise serum levels of cholesterol and triglycerides.

Hydrochlorothiazide may raise the serum uric acid level due to reduced clearance of uric acid and may cause or exacerbate hyperuricemia and precipitate gout in susceptible patients.

Hydrochlorothiazide decreases urinary calcium excretion and may cause elevations of serum calcium. Monitor calcium levels in patients with hypercalcemia receiving Exforge HCT.

5.10 Acute Myopia and Secondary Angle-Closure Glaucoma

Hydrochlorothiazide, a sulfonamide, can cause an idiosyncratic reaction, resulting in acute transient myopia and acute angle-closure glaucoma. Symptoms include acute onset of decreased visual acuity or ocular pain and typically occur within hours to weeks of drug initiation. Untreated acute angle-closure glaucoma can lead to permanent vision loss. The primary treatment is to discontinue hydrochlorothiazide as rapidly as possible. Prompt medical or surgical treatments may need to be considered if the intraocular pressure remains uncontrolled. Risk factors for developing acute angle-closure glaucoma may include a history of sulfonamide or penicillin allergy.

6 ADVERSE REACTIONS

6.1 Clinical Trials Experience

Because clinical studies are conducted under widely varying conditions, adverse reaction rates observed in the clinical studies of a drug cannot be directly compared to rates in the clinical studies of another drug and may not reflect the rates observed in clinical practice.

In the controlled trial of Exforge HCT, where only the maximum dose (10/320/25 mg) was evaluated, safety data were obtained in 582 patients with hypertension. Adverse reactions have generally been mild and transient in nature and have only infrequently required discontinuation of therapy.

The overall frequency of adverse reactions was similar between men and women, younger (< 65 years) and older (> 65 years) patients, and black and white patients. In the active controlled clinical trial, discontinuation because of adverse events occurred in 4.0% of patients treated with Exforge HCT 10/320/25 mg compared to 2.9% of patients treated with valsartan/HCTZ 320/25 mg, 1.6% of patients treated with amlodipine/valsartan 10/320 mg, and 3.4% of patients treated with HCTZ/amlodipine 25/10 mg. The most common reasons for discontinuation of therapy with Exforge HCT were dizziness (1.0%) and hypotension (0.7%).

The most frequent adverse events that occurred in the active controlled clinical trial in at least 2% of patients treated with Exforge HCT are presented in the following table.

Preferred Term | Aml/Val/HCTZ 10/320/25 mg N=582 n (%) | Val/HCTZ 320/25 mg N=559 n (%) | Aml/Val 10/320 mg N=566 n (%) | HCTZ/Aml 25/10 mg N=561 n (%)
Dizziness | 48 (8.2) | 40 (7.2) | 14 (2.5) | 23 (4.1)
Edema | 38 (6.5) | 8 (1.4) | 65 (11.5) | 63 (11.2)
Headache | 30 (5.2) | 31 (5.5) | 30 (5.3) | 40 (7.1)
Dyspepsia | 13 (2.2) | 5 (0.9) | 6 (1.1) | 2 (0.4)
Fatigue | 13 (2.2) | 15 (2.7) | 12 (2.1) | 8 (1.4)
Muscle spasms | 13 (2.2) | 7 (1.3) | 7 (1.2) | 5 (0.9)
Back pain | 12 (2.1) | 13 (2.3) | 5 (0.9) | 12 (2.1)
Nausea | 12 (2.1) | 7 (1.3) | 10 (1.8) | 12 (2.1)
Nasopharyngitis | 12 (2.1) | 13 (2.3) | 13 (2.3) | 12 (2.1)

Orthostatic events (orthostatic hypotension and postural dizziness) were seen in 0.5% of patients.

Valsartan

Valsartan has been evaluated for safety in more than 4000 hypertensive patients in clinical trials. In trials in which valsartan was compared to an ACE inhibitor with or without placebo, the incidence of dry cough was significantly greater in the ACE inhibitor group (7.9%) than in the groups who received valsartan (2.6%) or placebo (1.5%). In a 129-patient trial limited to patients who had dry cough when they had previously received ACE inhibitors, the incidences of cough in patients who received valsartan, HCTZ, or lisinopril were 20%, 19%, and 69%, respectively (p < 0.001).

Clinical Laboratory Test Findings

Clinical laboratory test findings for Exforge HCT were obtained in a controlled trial of Exforge HCT administered at the maximal dose of 10/320/25 mg compared to maximal doses of dual therapies, i.e., valsartan/HCTZ 320/25 mg, amlodipine/valsartan 10/320 mg, and HCTZ/amlodipine 25/10 mg. Findings for the components of Exforge HCT were obtained from other trials.

Creatinine: In heart failure patients, greater than 50% increases in creatinine were observed in 3.9% of valsartan-treated patients compared to 0.9% of placebo-treated patients. In post-myocardial infarction patients, doubling of serum creatinine was observed in 4.2% of valsartan-treated patients and 3.4% of captopril-treated patients.

Blood Urea Nitrogen (BUN): In hypertensive patients, greater than 50% increases in BUN were observed in 30% of Exforge HCT-treated patients compared to 29% of valsartan/HCTZ patients, 15.8% of amlodipine/valsartan patients, and 18.5% of HCTZ/amlodipine patients. In heart failure patients, greater than 50% increases in BUN were observed in 17% of valsartan-treated patients compared to 6% of placebo-treated patients [see Warnings and Precautions (5.4)].

Neutropenia: Neutropenia (< 1500/L) was observed in 1.9% of patients treated with valsartan and 0.8% of patients treated with placebo.

6.2 Postmarketing Experience

The following additional adverse reactions have been reported in postmarketing experience. Because these reactions are reported voluntarily from a population of uncertain size, it is not always possible to reliably estimate their frequency or establish a causal relationship to drug exposure.

Amlodipine

With amlodipine, gynecomastia has been reported infrequently and a causal relationship is uncertain. Jaundice and hepatic enzyme elevations (mostly consistent with cholestasis or hepatitis), in some cases severe enough to require hospitalization, have been reported in association with use of amlodipine.

Valsartan

The following additional adverse reactions have been reported in postmarketing experience with valsartan or valsartan/hydrochlorothiazide:

Blood and Lymphatic: Decrease in hemoglobin, decrease in hematocrit, neutropenia

Hypersensitivity: Angioedema has been reported. Some of these patients previously experienced angioedema with other drugs, including ACE inhibitors. Exforge HCT should not be re-administered to patients who have had angioedema.

Digestive: Elevated liver enzymes and reports of hepatitis

Musculoskeletal: Rhabdomyolysis

Renal: Impaired renal function, renal failure

Dermatologic: Alopecia, bullous dermatitis

Vascular: Vasculitis

Nervous System: Syncope

Hydrochlorothiazide

The following additional adverse reactions have been reported in postmarketing experience with hydrochlorothiazide:

Acute renal failure, renal disorder, aplastic anemia, erythema multiforme, pyrexia, muscle spasm, asthenia, acute angle-closure glaucoma, bone marrow failure, worsening of diabetes control, hypokalemia, blood lipids increased, hyponatremia, hypomagnesemia, hypercalcemia, hypochloremic alkalosis, impotence, visual impairment.

Pathological changes in the parathyroid gland of patients with hypercalcemia and hypophosphatemia have been observed in a few patients on prolonged thiazide therapy. If hypercalcemia occurs, further diagnostic evaluation is necessary.

Non-melanoma Skin Cancer: Hydrochlorothiazide is associated with an increased risk of non-melanoma skin cancer. In a study conducted in the Sentinel System, increased risk was predominantly for squamous cell carcinoma (SCC) and in white patients taking large cumulative doses. The increased risk for SCC in the overall population was approximately 1 additional case per 16,000 patients per year, and for white patients taking a cumulative dose of ≥ 50,000 mg the risk increase was approximately 1 additional SCC case for every 6700 patients per year.

7 DRUG INTERACTIONS

No drug interaction studies have been conducted with Exforge HCT and other drugs, although studies have been conducted with the individual components. A pharmacokinetic drug-drug interaction study has been conducted to address the potential for pharmacokinetic interaction between the triple combination, Exforge HCT, and the corresponding 3 double combinations. No clinically relevant interaction was observed.

Amlodipine

Impact of Other Drugs on Amlodipine

CYP3A Inhibitors

Coadministration with CYP3A inhibitors (moderate and strong) results in increased systemic exposure to amlodipine and may require dose reduction. Monitor for symptoms of hypotension and edema when amlodipine is coadministered with CYP3A inhibitors to determine the need for dose adjustment [see Clinical Pharmacology (12.3)].

CYP3A Inducers

No information is available on the quantitative effects of CYP3A inducers on amlodipine. Blood pressure should be closely monitored when amlodipine is coadministered with CYP3A inducers (e.g., rifampicin, St. John’s Wort).

Sildenafil

Monitor for hypotension when sildenafil is coadministered with amlodipine [see Clinical Pharmacology (12.2)].

Impact of Amlodipine on Other Drugs

Simvastatin

Coadministration of simvastatin with amlodipine increases the systemic exposure of simvastatin. Limit the dose of simvastatin in patients on amlodipine to 20 mg daily [see Clinical Pharmacology (12.3)].

Immunosuppressants

Amlodipine may increase the systemic exposure of cyclosporine or tacrolimus when coadministered. Frequent monitoring of trough blood levels of cyclosporine and tacrolimus is recommended and adjust the dose when appropriate [see Clinical Pharmacology (12.3)].

Valsartan

Agents Increasing Serum Potassium: Concomitant use of valsartan with other agents that block the renin-angiotensin system, potassium-sparing diuretics (e.g., spironolactone, triamterene, amiloride), potassium supplements, salt substitutes containing potassium or other drugs that may increase potassium levels (e.g., heparin) may lead to increases in serum potassium and in heart failure patients to increases in serum creatinine. If co-medication is considered necessary, monitoring of serum potassium is advisable.

Non-Steroidal Anti-Inflammatory (NSAID) Agents Including Selective Cyclooxygenase-2 Inhibitors (COX-2 Inhibitors): In patients who are elderly, volume-depleted (including those on diuretic therapy), or with compromised renal function, coadministration of NSAIDs, including selective COX-2 inhibitors, with angiotensin II receptor antagonists, including valsartan, may result in deterioration of renal function, including possible acute renal failure. These effects are usually reversible. Monitor renal function periodically in patients receiving valsartan and NSAID therapy.

The antihypertensive effect of angiotensin II receptor antagonists, including valsartan, may be attenuated by NSAIDs including selective COX-2 inhibitors.

Dual Blockade of the Renin-Angiotensin System (RAS): Dual blockade of the RAS with angiotensin receptor blockers, ACE inhibitors, or aliskiren is associated with increased risks of hypotension, hyperkalemia, and changes in renal function (including acute renal failure) compared to monotherapy. Most patients receiving the combination of two RAS inhibitors do not obtain any additional benefit compared to monotherapy. In general, avoid combined use of RAS inhibitors. Closely monitor blood pressure, renal function and electrolytes in patients on valsartan and other agents that affect the RAS.

Do not coadminister aliskiren with valsartan in patients with diabetes. Avoid use of aliskiren with valsartan in patients with renal impairment (GFR < 60 mL/min).

Valsartan – Hydrochlorothiazide

Lithium: Increases in serum lithium concentrations and lithium toxicity have been reported during concomitant administration of lithium with angiotensin II receptor antagonists or thiazides. Monitor lithium levels in patients taking Exforge HCT.

Hydrochlorothiazide

When administered concurrently, the following drugs may interact with thiazide diuretics:

Antidiabetic Drugs (oral agents and insulin): Dosage adjustment of the antidiabetic drug may be required.

Non-Steroidal Anti-inflammatory Drugs (NSAIDs and COX-2 selective inhibitors): When Exforge HCT and nonsteroidal anti-inflammatory agents are used concomitantly, the patient should be observed closely to determine if the desired effect of diuretic is obtained.

Carbamazepine: May lead to symptomatic hyponatremia.

Ion Exchange Resins: Staggering the dosage of hydrochlorothiazide and ion exchange resins (e.g., cholestyramine, colestipol) such that hydrochlorothiazide is administered at least 4 hours before or 4 to 6 hours after the administration of resins, would potentially minimize the interaction [see Clinical Pharmacology (12.3)].

Cyclosporine: Concomitant treatment with cyclosporine may increase the risk of hyperuricemia and gout-type complications.

8 USE IN SPECIFIC POPULATIONS

8.1 Pregnancy

Risk Summary

Exforge HCT can cause fetal harm when administered to a pregnant woman. Use of drugs that act on the renin-angiotensin system during the second and third trimesters of pregnancy reduces fetal renal function and increases fetal and neonatal morbidity and death. Most epidemiologic studies examining fetal abnormalities after exposure to antihypertensive use in the first trimester have not distinguished drugs affecting the renin-angiotensin system from other antihypertensive agents. Published reports include cases of anhydramnios and oligohydramnios in pregnant women treated with valsartan (see Clinical Considerations).

When pregnancy is detected, discontinue Exforge HCT as soon as possible.

The estimated background risk of major birth defects and miscarriage for the indicated population is unknown. All pregnancies have a background risk of birth defect, loss, or other adverse outcomes. In the U.S. general population, the estimated background risk of major birth defects and miscarriage in clinically recognized pregnancies is 2-4% and 15-20%, respectively.

Clinical Considerations

Disease-Associated Maternal and/or Embryo/Fetal Risk

Hypertension in pregnancy increases the maternal risk for pre-eclampsia, gestational diabetes, premature delivery, and delivery complications (e.g., need for cesarean section, and post-partum hemorrhage). Hypertension increases the fetal risk for intrauterine growth restriction and intrauterine death. Pregnant women with hypertension should be carefully monitored and managed accordingly.

Fetal/Neonatal Adverse Reactions

Valsartan

Oligohydramnios in pregnant women who use drugs affecting the renin-angiotensin system in the second and third trimesters of pregnancy can result in the following: reduced fetal renal function leading to anuria and renal failure, fetal lung hypoplasia, skeletal deformations, including skull hypoplasia, hypotension and death.

Perform serial ultrasound examinations to assess the intra-amniotic environment. Fetal testing may be appropriate, based on the week of gestation. Patients and physicians should be aware, however, that oligohydramnios may not appear until after the fetus has sustained irreversible injury. If oligohydramnios is observed, consider alternative drug treatment. Closely observe neonates with histories of in utero exposure to Exforge HCT for hypotension, oliguria, and hyperkalemia. In neonates with a history of in utero exposure to Exforge HCT, if oliguria or hypotension occurs, support blood pressure and renal perfusion. Exchange transfusions or dialysis may be required as a means of reversing hypotension and replacing renal function.

Hydrochlorothiazide

Thiazides can cross the placenta, and concentrations reached in the umbilical vein approach those in the maternal plasma. Hydrochlorothiazide, like other diuretics, can cause placental hypoperfusion. It accumulates in the amniotic fluid, with reported concentrations up to 19 times higher than in umbilical vein plasma. Use of thiazides during pregnancy is associated with a risk of fetal or neonatal jaundice or thrombocytopenia. Since they do not prevent or alter the course of EPH (Edema, Proteinuria, Hypertension) gestosis (preeclampsia), these drugs should not be used to treat hypertension in pregnant women. The use of HCTZ for other indications (e.g., heart disease) in pregnancy should be avoided.

Data

Animal Data

Valsartan and Amlodipine

In rats, administered 20 mg/kg/day amlodipine plus 320 mg/kg/day valsartan, treatment-related maternal and fetal effects (developmental delays and alterations noted in the presence of significant maternal toxicity) were noted with the high dose combination. This corresponds to dose multiples of 9 and 19.5 times, respectively, the maximum recommended human dose (MRHD) of 10 mg/day for amlodipine and 320 mg/day for valsartan (based on body surface area and considering a 60 kg patient).

Hydrochlorothiazide

No teratogenic effects were observed when hydrochlorothiazide was administered to mice and rats via gavage at doses of up to 3,000 and 1,000 mg/kg/day (608 and 405 times the MRHD), on gestation days 6 through 15.

8.2 Lactation

Risk Summary

There is limited information regarding the presence of Exforge HCT in human milk, the effects on the breastfed infant, or the effects on milk production. Hydrochlorothiazide is present in human milk and valsartan is present in rat milk. Limited published studies report that amlodipine is present in human milk. Because of the potential for serious adverse reactions in breastfed infants, advise a nursing woman that breastfeeding is not recommended during treatment with Exforge HCT.

Data

Valsartan was detected in the milk of lactating rats 15 minutes after oral administration of a 3 mg/kg dose.

8.4 Pediatric Use

The safety and effectiveness of Exforge HCT in pediatric patients have not been established.

8.5 Geriatric Use

Amlodipine

Clinical studies of amlodipine besylate tablets did not include sufficient numbers of subjects aged 65 and over to determine whether they respond differently from younger subjects. Other reported clinical experience has not identified differences in responses between the elderly and younger patients. In general, dose selection for an elderly patient should be cautious, usually starting at the low end of the dosing range, reflecting the greater frequency of decreased hepatic, renal or cardiac function, and of concomitant disease or other drug therapy. Elderly patients have decreased clearance of amlodipine with a resulting increase of AUC of approximately 40% to 60% [see Clinical Pharmacology (12.3)]. The recommended starting dose of amlodipine 2.5 mg is not an available strength with Exforge HCT [see Clinical Studies (14)].

8.6 Renal Impairment

Safety and effectiveness of Exforge HCT in patients with severe renal impairment (CrCl < 30 mL/min) have not been established. No dose adjustment is required in patients with mild (CrCl 60 to 90 mL/min) or moderate (CrCl 30 to 60 mL/min) renal impairment.

8.7 Hepatic Impairment

Amlodipine

Exposure to amlodipine is increased in patients with hepatic insufficiency. The recommended initial dose of amlodipine in patients with hepatic impairment is 2.5 mg, which is not an available strength with Exforge HCT [see Clinical Pharmacology (12.3)].

Valsartan

No dose adjustment is necessary for patients with mild-to-moderate disease. No dosing recommendations can be provided for patients with severe liver disease.

Hydrochlorothiazide

Minor alterations of fluid and electrolyte balance may precipitate hepatic coma in patients with impaired hepatic function or progressive liver disease.

10 OVERDOSAGE

Limited data are available related to overdosage in humans. The most likely manifestations of overdosage would be hypotension and tachycardia; bradycardia could occur from parasympathetic (vagal) stimulation. If symptomatic hypotension should occur, institute supportive treatment.

Amlodipine

Single oral doses of amlodipine maleate equivalent to 40 mg/kg and 100 mg/kg amlodipine in mice and rats, respectively, caused deaths. Single oral doses equivalent to 4 or more mg/kg amlodipine in dogs (11 or more times the MRHD on a mg/m^2 basis) caused a marked peripheral vasodilation and hypotension.

Overdosage might be expected to cause excessive peripheral vasodilation with marked hypotension. In humans, experience with intentional overdosage of amlodipine is limited. Marked and potentially prolonged systemic hypotension up to and including shock with fatal outcome have been reported.

If massive overdose should occur, initiate active cardiac and respiratory monitoring. Frequent blood pressure measurements are essential. Should hypotension occur, initiate cardiovascular support, including elevation of the extremities and the judicious administration of fluids. If hypotension remains unresponsive to these conservative measures, consider administration of vasopressors (such as phenylephrine) with attention to circulating volume and urine output. As amlodipine is highly protein bound, hemodialysis is not likely to be of benefit. Administration of activated charcoal to healthy volunteers immediately or up to two hours after ingestion of amlodipine has been shown to significantly decrease amlodipine absorption.

Valsartan

Depressed level of consciousness, circulatory collapse, and shock have been reported.

Valsartan is not removed from the plasma by hemodialysis.

Valsartan was without grossly observable adverse effects at single oral doses up to 2,000 mg/kg in rats and up to 1,000 mg/kg in marmosets, except for salivation and diarrhea in the rat and vomiting in the marmoset at the highest dose (60 and 31 times, respectively, the MRHD on a mg/m^2 basis) (calculations assume an oral dose of 320 mg/day and a 60-kg patient).

Hydrochlorothiazide

The degree to which hydrochlorothiazide is removed by hemodialysis has not been established. The most common signs and symptoms observed in patients are those caused by electrolyte depletion (hypokalemia, hypochloremia, hyponatremia) and dehydration resulting from excessive diuresis. If digitalis has also been administered, hypokalemia may accentuate cardiac arrhythmias.

The oral LD50 of hydrochlorothiazide is greater than 10 g/kg in both mice and rats, 2000 and 4000 times, respectively, the MRHD on a mg/m^2 basis (calculations assume an oral dose of 25 mg/day and a 60-kg patient).

Valsartan and Hydrochlorothiazide

In rats and marmosets, single oral doses of valsartan up to 1524 and 762 mg/kg in combination with hydrochlorothiazide at doses up to 476 and 238 mg/kg, respectively, were very well tolerated without any treatment-related effects. These no adverse effect doses in rats and marmosets, respectively, represent 46.5 and 23 times the MRHD of valsartan and 188 and 113 times the MRHD of hydrochlorothiazide on a mg/m^2 basis (calculations assume an oral dose of 320 mg/day valsartan in combination with 25 mg/day hydrochlorothiazide and a 60 kg patient).

11 DESCRIPTION

Exforge HCT is a fixed combination of amlodipine, valsartan, and hydrochlorothiazide.

Exforge HCT contains the besylate salt of amlodipine, a dihydropyridine calcium channel blocker (CCB). Amlodipine besylate, USP is a white to pale yellow crystalline powder, slightly soluble in water and sparingly soluble in ethanol. Amlodipine besylate’s chemical name is 3-Ethyl 5-methyl (±)-2-[(2-aminoethoxy)methyl]-4-(o-chlorophenyl)-1,4-dihydro-6-methyl-3,5-pyridinedicarboxylate, monobenzenesulfonate; its structural formula is:

Its empirical formula is C20H25ClN2O5•C6H6O3S and its molecular weight is 567.1.

Valsartan, USP is a nonpeptide, orally active, and specific angiotensin II antagonist acting on the AT1 receptor subtype. Valsartan is a white to practically white fine powder, soluble in ethanol and methanol and slightly soluble in water. Valsartan’s chemical name is N-(1-oxopentyl)-N-[[2′-(1H-tetrazol-5-yl)[1,1′-biphenyl]-4-yl]methyl]-L-valine; its structural formula is:

Its empirical formula is C24H29N5O3 and its molecular weight is 435.5.

Hydrochlorothiazide, USP is a white, or practically white, practically odorless, crystalline powder. It is slightly soluble in water; freely soluble in sodium hydroxide solution, in n-butylamine, and in dimethylformamide; sparingly soluble in methanol; and insoluble in ether, in chloroform, and in dilute mineral acids. Hydrochlorothiazide is chemically described as 6-chloro-3,4-dihydro-2H-1,2,4-benzothiadiazine-7-sulfonamide 1,1-dioxide.

Hydrochlorothiazide is a thiazide diuretic. Its empirical formula is C7H8ClN3O4S2, its molecular weight is 297.73, and its structural formula is:

Exforge HCT (amlodipine, valsartan, and hydrochlorothiazide) is available as film-coated tablets containing amlodipine besylate (6.9 mg or 13.9 mg, equivalent to 5 mg or 10 mg of amlodipine respectively), with valsartan 160 mg or 320 mg, and hydrochlorothiazide 12.5 mg or 25 mg, providing for the following available combinations: 5/160/12.5 mg, 10/160/12.5 mg, 5/160/25 mg, 10/160/25 mg, and 10/320/25 mg. The inactive ingredients for all strengths of the tablets include microcrystalline cellulose; crospovidone; colloidal anhydrous silica; magnesium stearate; hypromellose, macrogol 4000, and talc. Additionally, the 5/160/12.5 mg strength contains titanium dioxide; the 10/160/12.5 mg strength contains titanium dioxide and yellow and red iron oxides; the 5/160/25 mg strength contains titanium dioxide and yellow iron oxide, and the 10/160/25 mg and 10/320/25 mg strengths both contain yellow iron oxide.

12 CLINICAL PHARMACOLOGY

12.1 Mechanism of Action

The active ingredients of Exforge HCT target 3 separate mechanisms involved in blood pressure regulation. Specifically, amlodipine blocks the contractile effects of calcium on cardiac and vascular smooth muscle cells; valsartan blocks the vasoconstriction and sodium retaining effects of angiotensin II on cardiac, vascular smooth muscle, adrenal and renal cells; and hydrochlorothiazide directly promotes the excretion of sodium and chloride in the kidney leading to reductions in intravascular volume. A more detailed description of the mechanism of action of each individual component follows.

Amlodipine

Amlodipine is a dihydropyridine calcium channel blocker that inhibits the transmembrane influx of calcium ions into vascular smooth muscle and cardiac muscle. Experimental data suggest that amlodipine binds to both dihydropyridine and nondihydropyridine binding sites. The contractile processes of cardiac muscle and vascular smooth muscle are dependent upon the movement of extracellular calcium ions into these cells through specific ion channels. Amlodipine inhibits calcium ion influx across cell membranes selectively, with a greater effect on vascular smooth muscle cells than on cardiac muscle cells. Negative inotropic effects can be detected in vitro but such effects have not been seen in intact animals at therapeutic doses. Serum calcium concentration is not affected by amlodipine. Within the physiologic pH range, amlodipine is an ionized compound (pKa = 8.6), and its kinetic interaction with the calcium channel receptor is characterized by a gradual rate of association and dissociation with the receptor binding site, resulting in a gradual onset of effect.

Amlodipine is a peripheral arterial vasodilator that acts directly on vascular smooth muscle to cause a reduction in peripheral vascular resistance and reduction in blood pressure.

Valsartan

Angiotensin II is formed from angiotensin I in a reaction catalyzed by angiotensin-converting enzyme (ACE, kininase II). Angiotensin II is the principal pressor agent of the renin-angiotensin system, with effects that include vasoconstriction, stimulation of synthesis and release of aldosterone, cardiac stimulation, and renal reabsorption of sodium. Valsartan blocks the vasoconstrictor and aldosterone-secreting effects of angiotensin II by selectively blocking the binding of angiotensin II to the AT1 receptor in many tissues, such as vascular smooth muscle and the adrenal gland. Its action is therefore independent of the pathways for angiotensin II synthesis.

There is also an AT2 receptor found in many tissues, but AT2 is not known to be associated with cardiovascular homeostasis. Valsartan has much greater affinity (about 20,000-fold) for the AT1 receptor than for the AT2 receptor. The increased plasma levels of angiotensin following AT1 receptor blockade with valsartan may stimulate the unblocked AT2 receptor. The primary metabolite of valsartan is essentially inactive with an affinity for the AT1 receptor about one-200th that of valsartan itself.

Blockade of the renin-angiotensin system with ACE inhibitors, which inhibit the biosynthesis of angiotensin II from angiotensin I, is widely used in the treatment of hypertension. ACE inhibitors also inhibit the degradation of bradykinin, a reaction also catalyzed by ACE. Because valsartan does not inhibit ACE (kininase II), it does not affect the response to bradykinin. Whether this difference has clinical relevance is not yet known. Valsartan does not bind to or block other hormone receptors or ion channels known to be important in cardiovascular regulation.

Blockade of the angiotensin II receptor inhibits the negative regulatory feedback of angiotensin II on renin secretion, but the resulting increased plasma renin activity and angiotensin II circulating levels do not overcome the effect of valsartan on blood pressure.

Hydrochlorothiazide

Hydrochlorothiazide is a thiazide diuretic. Thiazides affect the renal tubular mechanisms of electrolyte reabsorption, directly increasing excretion of sodium and chloride in approximately equivalent amounts. Indirectly, the diuretic action of hydrochlorothiazide reduces plasma volume, with consequent increases in plasma renin activity, increases in aldosterone secretion, increases in urinary potassium loss, and decreases in serum potassium. The renin-aldosterone link is mediated by angiotensin II, so coadministration of an angiotensin II receptor antagonist tends to reverse the potassium loss associated with these diuretics.

The mechanism of the antihypertensive effect of thiazides is unknown.

12.2 Pharmacodynamics

Exforge HCT has been shown to be effective in lowering blood pressure. The 3 components of Exforge HCT (amlodipine, valsartan, hydrochlorothiazide) lower the blood pressure through complementary mechanisms, each working at a separate site and blocking different effector pathways. The pharmacodynamics of each individual component are described below.

Exforge HCT has not been studied in indications other than hypertension.

Amlodipine

Following administration of therapeutic doses to patients with hypertension, amlodipine produces vasodilation resulting in a reduction of supine and standing blood pressures. These decreases in blood pressure are not accompanied by a significant change in heart rate or plasma catecholamine levels with chronic dosing. Although the acute intravenous administration of amlodipine decreases arterial blood pressure and increases heart rate in hemodynamic studies of patients with chronic stable angina, chronic oral administration of amlodipine in clinical trials did not lead to clinically significant changes in heart rate or blood pressures in normotensive patients with angina.

With chronic, once-daily administration, antihypertensive effectiveness is maintained for at least 24 hours. Plasma concentrations correlate with effect in both young and elderly patients. The magnitude of reduction in blood pressure with amlodipine is also correlated with the height of pretreatment elevation; thus, individuals with moderate hypertension (diastolic pressure 105-114 mmHg) had about a 50% greater response than patients with mild hypertension (diastolic pressure 90-104 mmHg). Normotensive subjects experienced no clinically significant change in blood pressure (+1/-2 mmHg).

In hypertensive patients with normal renal function, therapeutic doses of amlodipine resulted in a decrease in renal vascular resistance and an increase in glomerular filtration rate and effective renal plasma flow without change in filtration fraction or proteinuria.

As with other calcium channel blockers, hemodynamic measurements of cardiac function at rest and during exercise (or pacing) in patients with normal ventricular function treated with amlodipine have generally demonstrated a small increase in cardiac index without significant influence on dP/dt or on left ventricular end diastolic pressure or volume. In hemodynamic studies, amlodipine has not been associated with a negative inotropic effect when administered in the therapeutic dose range to intact animals and man, even when coadministered with beta-blockers to man. Similar findings, however, have been observed in normal or well-compensated patients with heart failure with agents possessing significant negative inotropic effects.

Amlodipine does not change sinoatrial nodal function or atrioventricular conduction in intact animals or man. In patients with chronic stable angina, intravenous administration of 10 mg did not significantly alter A-H and H-V conduction and sinus node recovery time after pacing. Similar results were obtained in patients receiving amlodipine and concomitant beta-blockers. In clinical studies in which amlodipine was administered in combination with beta-blockers to patients with either hypertension or angina, no adverse effects of electrocardiographic (ECG) parameters were observed. In clinical trials with angina patients alone, amlodipine therapy did not alter ECG intervals or produce higher degrees of AV blocks.

Amlodipine has indications other than hypertension which are described in its full prescribing information.

Drug Interactions

Sildenafil

When amlodipine and sildenafil were used in combination, each agent independently exerted its own blood pressure lowering effect [see Drug Interactions (7)].

Valsartan

Valsartan inhibits the pressor effect of angiotensin II infusions. An oral dose of 80 mg inhibits the pressor effect by about 80% at peak with approximately 30% inhibition persisting for 24 hours. No information on the effect of larger doses is available.

Removal of the negative feedback of angiotensin II causes a 2- to 3-fold rise in plasma renin and consequent rise in angiotensin II plasma concentration in hypertensive patients. Minimal decreases in plasma aldosterone were observed after administration of valsartan; very little effect on serum potassium was observed.

Administration of valsartan to patients with essential hypertension results in a significant reduction of sitting, supine, and standing systolic blood pressure, usually with little or no orthostatic change.

Valsartan has indications other than hypertension which are described in its full prescribing information.

Hydrochlorothiazide

After oral administration of hydrochlorothiazide, diuresis begins within 2 hours, peaks in about 4 hours and lasts about 6 to 12 hours.

12.3 Pharmacokinetics

Exforge HCT

Following oral administration of Exforge HCT in normal healthy adults, peak plasma concentrations of amlodipine, valsartan, and HCTZ are reached in about 6 hours, 3 hours, and 2 hours, respectively. The rate and extent of absorption of amlodipine, valsartan, and HCTZ from Exforge HCT are the same as when administered as individual dosage forms.

The bioavailability of amlodipine, valsartan, and HCTZ were not altered when Exforge HCT was administered with food. Exforge HCT may be administered with or without food.

Amlodipine

Peak plasma concentrations of amlodipine are reached 6 to 12 hours after administration of amlodipine alone. Absolute bioavailability has been estimated to be between 64% and 90%. The apparent volume of distribution of amlodipine is 21 L/kg. Approximately 93% of circulating amlodipine is bound to plasma proteins in hypertensive patients.

Amlodipine is extensively (about 90%) converted to inactive metabolites via hepatic metabolism with 10% of the parent compound and 60% of the metabolites excreted in the urine.

Elimination of amlodipine from the plasma is biphasic with a terminal elimination half-life of about 30 to 50 hours. Steady state plasma levels of amlodipine are reached after 7 to 8 days of consecutive daily dosing.

Valsartan

Following oral administration of valsartan alone, peak plasma concentrations of valsartan are reached in 2 to 4 hours. Absolute bioavailability is about 25% (range 10% to 35%).

The steady state volume of distribution of valsartan after intravenous administration is 17 L indicating that valsartan does not distribute into tissues extensively. Valsartan is highly bound to serum proteins (95%), mainly serum albumin.

Valsartan shows biexponential decay kinetics following intravenous administration with an average elimination half-life of about 6 hours. The recovery is mainly as unchanged drug, with only about 20% of dose recovered as metabolites. The primary metabolite, accounting for about 9% of dose, is valeryl 4-hydroxy valsartan. In vitro metabolism studies involving recombinant CYP450 enzymes indicated that the CYP2C9 isoenzyme is responsible for the formation of valeryl-4-hydroxy valsartan. Valsartan does not inhibit CYP450 isozymes at clinically relevant concentrations. CYP450 mediated drug interaction between valsartan and coadministered drugs are unlikely because of the low extent of metabolism.

Valsartan, when administered as an oral solution, is primarily recovered in feces (about 83% of dose) and urine (about 13% of dose). Following intravenous administration, plasma clearance of valsartan is about 2 L/h and its renal clearance is 0.62 L/h (about 30% of total clearance).

Hydrochlorothiazide

The estimated absolute bioavailability of hydrochlorothiazide after oral administration is about 70%. Peak plasma hydrochlorothiazide concentrations (Cmax) are reached within 2 to 5 hours after oral administration. There is no clinically significant effect of food on the bioavailability of hydrochlorothiazide.

Hydrochlorothiazide binds to albumin (40% to 70%) and distributes into erythrocytes. Following oral administration, plasma hydrochlorothiazide concentrations decline biexponentially, with a mean distribution half-life of about 2 hours and an elimination half-life of about 10 hours.

About 70% of an orally administered dose of hydrochlorothiazide is eliminated in the urine as unchanged drug.

Specific Populations

Geriatric: Elderly patients have decreased clearance of amlodipine with a resulting increase in peak plasma levels, elimination half-life, and AUC. Exposure (measured by AUC) to valsartan is higher by 70% and the half-life is longer by 35% in the elderly than in the young. Limited amount of data suggest that the systemic clearance of hydrochlorothiazide is reduced in both healthy and hypertensive elderly subjects compared to young healthy volunteers.

Gender: Pharmacokinetics of valsartan do not differ significantly between males and females.

Race: Pharmacokinetic differences due to race have not been studied.

Renal Insufficiency: The pharmacokinetics of amlodipine are not significantly influenced by renal impairment. There is no apparent correlation between renal function (measured by creatinine clearance) and exposure (measured by AUC) to valsartan in patients with different degrees of renal impairment. Valsartan has not been studied in patients with severe impairment of renal function (creatinine clearance <10 mL/min). Valsartan is not removed from the plasma by hemodialysis.

In a study in individuals with impaired renal function, the mean elimination half-life of hydrochlorothiazide was doubled in individuals with mild/moderate renal impairment (30 < CrCl < 90 mL/min) and tripled in severe renal impairment (CrCl ≤ 30 mL/min), compared to individuals with normal renal function (CrCl > 90 mL/min) [see Use in Specific Populations (8.6)].

Hepatic Insufficiency: Patients with hepatic insufficiency have decreased clearance of amlodipine with resulting increase in AUC of approximately 40% to 60%. On average, patients with mild-to-moderate chronic liver disease have twice the exposure (measured by AUC values) to valsartan of healthy volunteers (matched by age, sex, and weight) [see Use in Specific Populations (8.7)].

Drug Interactions

Amlodipine:

In vitro data in human plasma indicate that amlodipine has no effect on the protein binding of digoxin, phenytoin, warfarin, and indomethacin.

Impact of Other Drugs on Amlodipine

Coadministered cimetidine, magnesium-and aluminum hydroxide antacids, sildenafil, and grapefruit juice have no impact on the exposure to amlodipine.

CYP3A Inhibitors: Coadministration of a 180 mg daily dose of diltiazem with 5 mg amlodipine in elderly hypertensive patients resulted in a 60% increase in amlodipine systemic exposure. Erythromycin coadministration in healthy volunteers did not significantly change amlodipine systemic exposure. However, strong inhibitors of CYP3A (e.g., itraconazole, clarithromycin) may increase the plasma concentrations of amlodipine to a greater extent [see Drug Interactions (7)].

Impact of Amlodipine on Other Drugs

Coadministered amlodipine does not affect the exposure to atorvastatin, digoxin, ethanol and the warfarin prothrombin response time.

Simvastatin: Coadministration of multiple doses of 10 mg of amlodipine with 80 mg simvastatin resulted in a 77% increase in exposure to simvastatin compared to simvastatin alone [see Drug Interactions (7)].

Cyclosporine: A prospective study in renal transplant patients (N = 11) showed on an average of 40% increase in trough cyclosporine levels when concomitantly treated with amlodipine [see Drug Interactions (7)].

Tacrolimus: A prospective study in healthy Chinese volunteers (N = 9) with CYP3A5 expressers showed a 2.5- to 4-fold increase in tacrolimus exposure when concomitantly administered with amlodipine compared to tacrolimus alone. This finding was not observed in CYP3A5 non-expressers (N = 6). However, a 3-fold increase in plasma exposure to tacrolimus in a renal transplant patient (CYP3A5 non-expresser) upon initiation of amlodipine for the treatment of post-transplant hypertension resulting in reduction of tacrolimus dose has been reported. Irrespective of the CYP3A5 genotype status, the possibility of an interaction cannot be excluded with these drugs [see Drug Interactions (7)].

Valsartan:

No clinically significant pharmacokinetic interactions were observed when Diovan (valsartan) was coadministered with amlodipine, atenolol, cimetidine, digoxin, furosemide, glyburide, hydrochlorothiazide, or indomethacin. The valsartan-atenolol combination was more antihypertensive than either component, but it did not lower the heart rate more than atenolol alone.

Coadministration of valsartan and warfarin did not change the pharmacokinetics of valsartan or the time-course of the anticoagulant properties of warfarin.

Transporters: The results from an in vitro study with human liver tissue indicate that valsartan is a substrate of the hepatic uptake transporter OATP1B1 and the hepatic efflux transporter MRP2. Coadministration of inhibitors of the uptake transporter (rifampin, cyclosporine) or efflux transporter (ritonavir) may increase the systemic exposure to valsartan.

Hydrochlorothiazide:

Drugs That Alter Gastrointestinal Motility: The bioavailability of thiazide-type diuretics may be increased by anticholinergic agents (e.g., atropine, biperiden), apparently due to a decrease in gastrointestinal motility and the stomach emptying rate. Conversely, pro-kinetic drugs may decrease the bioavailability of thiazide diuretics.

Cholestyramine: In a dedicated drug interaction study, administration of cholestyramine 2 hours before hydrochlorothiazide resulted in a 70% reduction in exposure to hydrochlorothiazide. Further, administration of hydrochlorothiazide 2 hours before cholestyramine resulted in 35% reduction in exposure to hydrochlorothiazide.

Antineoplastic Agents (e.g., cyclophosphamide, methotrexate): Concomitant use of thiazide diuretics may reduce renal excretion of cytotoxic agents and enhance their myelosuppressive effects.

Alcohol, Barbiturates, or Narcotics: Potentiation of orthostatic hypotension may occur.

Skeletal Muscle Relaxants: Possible increased responsiveness to muscle relaxants, such as curare derivatives.

Digitalis Glycosides: Thiazide-induced hypokalemia or hypomagnesemia may predispose the patient to digoxin toxicity.

13 NONCLINICAL TOXICOLOGY

13.1 Carcinogenesis, Mutagenesis, Impairment of Fertility

Studies with Amlodipine/Valsartan/Hydrochlorothiazide: No carcinogenicity, mutagenicity, or fertility studies have been conducted with this combination. However, these studies have been conducted for amlodipine, valsartan, and hydrochlorothiazide alone. Based on the preclinical safety and human pharmacokinetic studies, there is no indication of any toxicologically significant adverse interaction between these components.

Studies with Amlodipine: Rats and mice treated with amlodipine maleate in the diet for up to two years, at concentrations calculated to provide daily dosage levels of 0.5, 1.25, and 2.5 mg amlodipine/kg/day, showed no evidence of a carcinogenic effect of the drug. For the mouse, the highest dose was, on a mg/m^2 basis, similar to the MRHD of 10 mg amlodipine/day. For the rat, the highest dose was, on a mg/m^2 basis, about 2.5 times the MRHD (calculations based on a 60 kg patient).

Mutagenicity studies conducted with amlodipine maleate revealed no drug-related effects at either the gene or chromosome level.

There was no effect on the fertility of rats treated orally with amlodipine maleate (males for 64 days and females for 14 days prior to mating) at doses of up to 10 mg amlodipine/kg/day (about 10 times the MRHD of 10 mg/day on a mg/m^2 basis).

Studies with Valsartan: There was no evidence of carcinogenicity when valsartan was administered in the diet to mice and rats for up to 2 years at concentrations calculated to provide doses of up to 160 and 200 mg/kg/day, respectively. These doses in mice and rats are about 2.4 and 6 times, respectively, the MRHD of 320 mg/day on a mg/m^2 basis (calculations based on a 60 kg patient).

Mutagenicity assays did not reveal any valsartan-related effects at either the gene or chromosome level. These assays included bacterial mutagenicity tests with Salmonella and E. coli, a gene mutation test with Chinese hamster V79 cells, a cytogenetic test with Chinese hamster ovary cells, and a rat micronucleus test.

Valsartan had no adverse effects on the reproductive performance of male or female rats at oral doses of up to 200 mg/kg/day. This dose is about 6 times the MRHD on a mg/m^2 basis.

Studies with Hydrochlorothiazide: Two-year feeding studies in mice and rats conducted under the auspices of the National Toxicology Program (NTP) uncovered no evidence of a carcinogenic potential of hydrochlorothiazide in female mice (at doses of up to approximately 600 mg/kg/day) or in male and female rats (at doses of up to approximately 100 mg/kg/day). The NTP, however, found equivocal evidence for hepatocarcinogenicity in male mice.

Hydrochlorothiazide was not genotoxic in vitro in the Ames mutagenicity assay of Salmonella Typhimurium strains TA 98, TA 100, TA 1535, TA 1537, and TA 1538 and in the Chinese Hamster Ovary (CHO) test for chromosomal aberrations, or in vivo in assays using mouse germinal cell chromosomes, Chinese hamster bone marrow chromosomes, and the Drosophila sex-linked recessive lethal trait gene. Positive test results were obtained in the in vitro CHO Sister Chromatid Exchange (clastogenicity) and Mouse Lymphoma Cell (mutagenicity) assays and in the Aspergillus Nidulans non-disjunction assay.

Hydrochlorothiazide had no adverse effects on the fertility of mice and rats of either sex in studies wherein these species were exposed via diet at doses of up to 100 and 4 mg/kg, respectively, prior to mating and throughout gestation. These doses of hydrochlorothiazide in mice and rats are 19 and 1.5 times, respectively, the MRHD on a mg/m^2 basis (calculations assume an oral dose of 25 mg/day and a 60-kg patient).

14 CLINICAL STUDIES

Exforge HCT was studied in a double-blind, active controlled study in hypertensive patients. A total of 2271 patients with moderate to severe hypertension (mean baseline systolic/diastolic blood pressure was 170/107 mmHg) received treatments of amlodipine/valsartan/HCTZ 10/320/25 mg, valsartan/HCTZ 320/25 mg, amlodipine/valsartan 10/320 mg, or HCTZ/amlodipine 25/10 mg. At study initiation, patients assigned to the 2-component arms received lower doses of their treatment combination while patients assigned to the Exforge HCT arm received 160/12.5 mg valsartan/hydrochlorothiazide. After 1 week, Exforge HCT patients were titrated to 5/160/12.5 mg amlodipine/valsartan/hydrochlorothiazide, while all other patients continued receiving their initial doses. After 2 weeks, all patients were titrated to their full treatment dose. A total of 55% of patients were male, 14% were 65 years or older, 72% were Caucasian, and 17% were black.

At Week 8, the triple combination therapy produced greater reductions in blood pressure than each of the 3 dual combination treatments (p < 0.0001 for both diastolic and systolic blood pressures reductions). The reductions in systolic/diastolic blood pressure with Exforge HCT were 7.6/5.0 mmHg greater than with valsartan/HCTZ, 6.2/3.3 mmHg greater than with amlodipine/valsartan, and 8.2/5.3 mmHg greater than with amlodipine/HCTZ (see Figure 1). The full blood pressure lowering effect was achieved 2 weeks after being on the maximal dose of Exforge HCT (see Figure 2 and Figure 3). As the pivotal study was an active-controlled trial, the treatment effects shown in Figures 1, 2, and 3 include a placebo effect of unknown size.

Figure 1: Reduction in Mean Blood Pressure at Endpoint
Figure 2: Mean Sitting Diastolic Blood Pressure by Treatment and Week
Figure 3: Mean Sitting Systolic Blood Pressure by Treatment and Week

A subgroup of 283 patients was studied with ambulatory blood pressure monitoring. The blood pressure lowering effect in the triple therapy group was maintained throughout the 24-hour period (see Figure 4 and Figure 5).

Figure 4: Mean Ambulatory Diastolic Blood Pressure at Endpoint by Treatment and Hour
Figure 5: Mean Ambulatory Systolic Blood Pressure at Endpoint by Treatment and Hour

There are no trials of the Exforge HCT combination tablet demonstrating reductions in cardiovascular risk in patients with hypertension, but both the amlodipine and hydrochlorothiazide components and several ARBs, which are the same pharmacological class as the valsartan component, have demonstrated such benefits.

16 HOW SUPPLIED/STORAGE AND HANDLING

Exforge HCT (amlodipine, valsartan, and hydrochlorothiazide) is available as film-coated tablets containing amlodipine besylate (6.9 mg or 13.9 mg, equivalent to 5 mg or 10 mg of amlodipine respectively), with valsartan 160 mg or 320 mg, and hydrochlorothiazide 12.5 mg or 25 mg, providing for the following available combinations: 5/160/12.5 mg, 10/160/12.5 mg, 5/160/25 mg, 10/160/25 mg, and 10/320/25 mg. All strengths are packaged in bottles of 30 tablets.

5 mg amlodipine/160 mg valsartan /12.5 mg hydrochlorothiazide tablets – White, non-scored, film-coated tablet, ovaloid, biconvex with beveled edge with debossing “NVR” on one side and “VCL” on the other side.

Bottles of 30 NDC 0078-0559-15

10 mg amlodipine/160 mg valsartan /12.5 mg hydrochlorothiazide tablets – Pale yellow, non-scored, film-coated tablet, ovaloid, biconvex with beveled edge with debossing “NVR” on one side and “VDL” on the other side.

Bottles of 30 NDC 0078-0561-15

5 mg amlodipine/160 mg valsartan /25 mg hydrochlorothiazide tablets – Yellow, non-scored, film-coated tablet, ovaloid, biconvex with beveled edge with debossing “NVR” on one side and “VEL” on the other side.

Bottles of 30 NDC 0078-0560-15

10 mg amlodipine/160 mg valsartan /25 mg hydrochlorothiazide tablets – Brown-yellow, non-scored, film-coated tablet, ovaloid, biconvex with beveled edge with debossing “NVR” on one side and “VHL” on the other side.

Bottles of 30 NDC 0078-0562-15

10 mg amlodipine/320 mg valsartan /25 mg hydrochlorothiazide tablets – Brown-yellow, non-scored, film-coated tablet, ovaloid, biconvex with beveled edge with debossing “NVR” on one side and “VFL” on the other side.

Bottles of 30 NDC 0078-0563-15

Store at 20°C to 25°C (68°F to 77°F); excursions permitted between 15°C and 30°C (59°F and 86°F) [see USP controlled room temperature].

Protect from moisture.

Dispense in tight container (USP).

17 PATIENT COUNSELING INFORMATION

Advise the patient to read the FDA-approved patient labeling (Patient Information).

Pregnancy: Advise female patients of childbearing age about the consequences of exposure to Exforge HCT during pregnancy. Discuss treatment options with women planning to become pregnant. Ask patients to report pregnancies to their physicians as soon as possible [see Warnings and Precautions (5.1) and Use in Specific Populations (8.1)]

Lactation: Advise women not to breastfeed during treatment with Exforge HCT [see Use in Specific Populations (8.2)].

Symptomatic Hypotension: Advise patients that lightheadedness can occur, especially during the first days of therapy, and that it should be reported to their healthcare provider. Tell patients that if syncope occurs to discontinue Exforge HCT until the physician has been consulted. Caution all patients that inadequate fluid intake, excessive perspiration, diarrhea, or vomiting can lead to an excessive fall in blood pressure, with the same consequences of lightheadedness and possible syncope [see Warnings and Precautions (5.2)].

Potassium Supplements: Advise patients not to use salt substitutes without consulting their healthcare provider [see Drug Interactions (7)].

Non-melanoma Skin Cancer: Instruct patients taking hydrochlorothiazide to protect skin from the sun and undergo regular skin cancer screening [see Adverse Reactions (6.2)].

T2021-12

Information for Patients

Patient Information

Exforge HCT® (X-phorj HCT)
(amlodipine, valsartan, and hydrochlorothiazide) Tablets

Read the Patient Information that comes with EXFORGE HCT before you start taking it and each time you get a refill. There may be new information. This leaflet does not take the place of talking with your doctor about your medical condition or treatment.

What is the most important information I should know about EXFORGE HCT?

- EXFORGE HCT can cause harm or death to an unborn baby.
- Talk to your doctor about other ways to lower your blood pressure if you plan to become pregnant.
- If you get pregnant while taking EXFORGE HCT, tell your doctor right away.

What is EXFORGE HCT?

EXFORGE HCT contains 3 prescription medicines:

1. amlodipine, a calcium channel blocker
2. valsartan, an angiotensin receptor blocker, and
3. hydrochlorothiazide, a diuretic (water pill)

EXFORGE HCT may be used to lower blood pressure in adults when 2 medicines to lower your high blood pressure are not enough.

EXFORGE HCT has not been studied in children under 18 years of age.

Who should not take EXFORGE HCT?

Do not take EXFORGE HCT if you have low or no urine output (anuria).

What should I tell my doctor before taking EXFORGE HCT?

Tell your doctor about all of your medical conditions, including if you:

- are pregnant or plan to become pregnant. See “What is the most important information I should know about EXFORGE HCT?”
- are breastfeeding or plan to breastfeed. EXFORGE HCT is present in human milk. It is not known whether EXFORGE HCT affects your breastfed baby or milk production. Do not breastfeed while you are taking EXFORGE HCT.
- are allergic to any of the ingredients in EXFORGE HCT. See the end of this leaflet for a list of the ingredients in EXFORGE HCT.
- have heart problems
- have liver problems
- have kidney problems
- are vomiting or having a lot of diarrhea
- have or had gallstones
- have Lupus
- have low levels of potassium (with or without symptoms such as muscle weakness, muscle spasms, abnormal heart rhythm) or magnesium in your blood
- have high levels of calcium in your blood (with or without symptoms such as nausea, vomiting, constipation, stomach pain, frequent urination, thirst, muscle weakness, and twitching).
- have high levels of uric acid in the blood.
- have ever had a reaction called angioedema, to another blood pressure medicine. Angioedema causes swelling of the face, lips, tongue, and may cause difficulty breathing.

Tell your doctor about all the medicines you take, including prescription and nonprescription medicines, vitamins, and herbal supplements. Some of your other medicines and EXFORGE HCT could affect each other, causing serious side effects.

Especially tell your doctor if you take:

- simvastatin or other cholesterol-lowering medicine
- other medicines for high blood pressure or a heart problem
- water pills (“diuretics”)
- potassium supplements. Your doctor may check the amount of potassium in your blood periodically.
- salt substitute containing potassium. Your doctor may check the amount of potassium in your blood periodically.
- diabetes medicine, including insulin
- narcotic pain medicines
- sleeping pills and antiseizure medicines called barbiturates
- lithium, a medicine used to treat some types of depression
- aspirin or other medicines called nonsteroidal anti-inflammatory drugs (NSAIDs), like ibuprofen or naproxen
- steroids
- alcohol
- digoxin or other digitalis glycosides (a heart medicine)
- muscle relaxants (medicines used during operations)
- certain cancer medicines, like cyclophosphamide or methotrexate
- medicines used to prevent and treat fungal infections (such as ketoconazole, itraconazole)
- medicines used to treat bacterial infections (such as clarithromycin, telithromycin)
- certain antibiotics (rifamycin group), a drug used to protect against transplant rejection (cyclosporine) or an antiretroviral drug used to treat HIV/AIDS infection (ritonavir). These drugs may increase the effect of valsartan.

Know the medicines you take. Keep a list of your medicines and show it to your doctor or pharmacist when you get a new medicine.

How should I take EXFORGE HCT?

- Take EXFORGE HCT exactly as your doctor tells you.
- Take EXFORGE HCT one time each day.
- EXFORGE HCT can be taken with or without food.
- If you miss a dose, take it as soon as you remember. If it is close to your next dose, do not take the missed dose. Just take the next dose at the regular time.
- If you take too much EXFORGE HCT, call your doctor or Poison Control Center, or go to the emergency room.
- Tell all your doctors and dentist you are taking EXFORGE HCT. This is especially important if you:
  - are going to have surgery
  - go for kidney dialysis

What are the possible side effects of EXFORGE HCT?

EXFORGE HCT may cause serious side effects including:

- harm to an unborn baby causing injury or death. See “What is the most important information I should know about EXFORGE HCT?”
- low blood pressure (hypotension). Low blood pressure is most likely to happen if you:
  - take water pills
  - are on a low-salt diet
  - have heart problems
  - get dialysis treatments
  - get sick with vomiting or diarrhea
  - drink alcohol

Lie down if you feel faint or dizzy. If you faint (lose consciousness), stop taking EXFORGE HCT. Call your doctor right away.

- Get emergency help if you get worse chest pain or chest pain that does not go away.
- kidney problems. Kidney problems may become worse in people that already have kidney disease. Some people will have changes in blood tests for kidney function and may need a lower dose of EXFORGE HCT. Call your doctor if you have swelling in your feet, ankles, or hands, or unexplained weight gain. If you have heart failure, your doctor should check your kidney function before prescribing EXFORGE HCT.
- laboratory blood test changes in people with heart failure. Some people with heart failure who take valsartan, one of the medicines in EXFORGE HCT, have changes in blood tests including increased potassium and decreased kidney function.
- allergic reactions
- skin rash. Call your doctor right away if you get an unusual skin rash.
- eye problems. One of the medicines in EXFORGE HCT can cause eye problems that may lead to vision loss. Symptoms of eye problems can happen within hours to weeks of starting EXFORGE HCT. Tell your doctor right away if you have:
  - decrease in vision
  - eye pain

The most common side effects of EXFORGE HCT include:

- dizziness
- swelling (edema) of the hands, ankles, or feet
- headache
- indigestion
- tiredness
- muscle spasms
- back pain
- nausea

Protect your skin from the sun and undergo regular skin cancer screening, as one of the medicines in EXFORGE HCT may cause non-melanoma skin cancer.

Tell your doctor if you have any side effect that bothers you or that does not go away.

These are not all the possible side effects of EXFORGE HCT. For more information, ask your doctor or pharmacist.

Call your doctor for medical advice about side effects. You may report side effects to FDA at 1-800-FDA-1088.

How should I store EXFORGE HCT?

- Store EXFORGE HCT at room temperature between 59°F and 86°F (15°C and 30°C).
- Keep EXFORGE HCT dry (protect it from moisture).

Keep EXFORGE HCT and all medicines out of the reach of children.

General Information about EXFORGE HCT

Medicines are sometimes prescribed for conditions that are not mentioned in the patient information leaflet. Do not use EXFORGE HCT for a condition for which it was not prescribed. Do not give EXFORGE HCT to other people, even if they have the same symptoms that you have. It may harm them.

This patient information leaflet summarizes the most important information about EXFORGE HCT. If you would like more information about EXFORGE HCT, talk with your doctor. You can ask your doctor or pharmacist for information about EXFORGE HCT that is written for health professionals. For more information, call 1-888-669-6682.

What are the ingredients in EXFORGE HCT?

Active ingredients: amlodipine besylate, valsartan, and hydrochlorothiazide

The inactive ingredients of all strengths of the tablets are crospovidone, magnesium stearate, microcrystalline cellulose, and colloidal anhydrous silica. The film coating contains hypromellose, talc, macrogol 4000, and may contain titanium dioxide or yellow and red iron oxides.

What is high blood pressure (hypertension)?

Blood pressure is the force of blood in your blood vessels when your heart beats and when your heart rests. You have high blood pressure when the force is too much. EXFORGE HCT can help your blood vessels relax so your blood pressure is lower. Medicines that lower blood pressure lower your chance of having a stroke or heart attack.

High blood pressure makes the heart work harder to pump blood throughout the body and causes damage to blood vessels. If high blood pressure is not treated, it can lead to stroke, heart attack, heart failure, kidney failure, and vision problems.

Distributed by:
Novartis Pharmaceuticals Corporation
East Hanover, New Jersey 07936

© Novartis

T2024-83
Revised: December 2024

PRINCIPAL DISPLAY PANEL

NDC 0078-0559-15

EXFORGE HCT®

amlodipine, valsartan, and
hydrochlorothiazide tablets

5 mg* / 160 mg / 12.5 mg

*each tablet contains 6.9 mg of amlodipine besylate

30 Tablets

Rx only

NOVARTIS

PRINCIPAL DISPLAY PANEL

NDC 0078-0560-15

EXFORGE HCT®

amlodipine, valsartan, and
hydrochlorothiazide tablets

5 mg* / 160 mg / 25 mg

*each tablet contains 6.9 mg of amlodipine besylate

30 Tablets

Rx only

NOVARTIS

PRINCIPAL DISPLAY PANEL

NDC 0078-0561-15

EXFORGE HCT®

amlodipine, valsartan, and
hydrochlorothiazide tablets

10 mg* / 160 mg / 12.5 mg

*each tablet contains 13.9 mg of amlodipine besylate

30 Tablets

Rx only

NOVARTIS

PRINCIPAL DISPLAY PANEL

NDC 0078-0562-15

EXFORGE HCT®

amlodipine, valsartan, and
hydrochlorothiazide tablets

10 mg* / 160 mg / 25 mg

*each tablet contains 13.9 mg of amlodipine besylate

30 Tablets

Rx only

NOVARTIS

PRINCIPAL DISPLAY PANEL

NDC 0078-0563-15

EXFORGE HCT®

amlodipine, valsartan, and
hydrochlorothiazide tablets

10 mg* / 320 mg / 25 mg

*each tablet contains 13.9 mg of amlodipine besylate

30 Tablets

Rx only

NOVARTIS